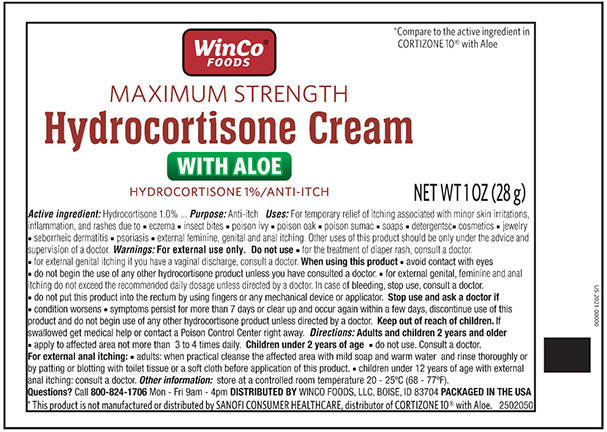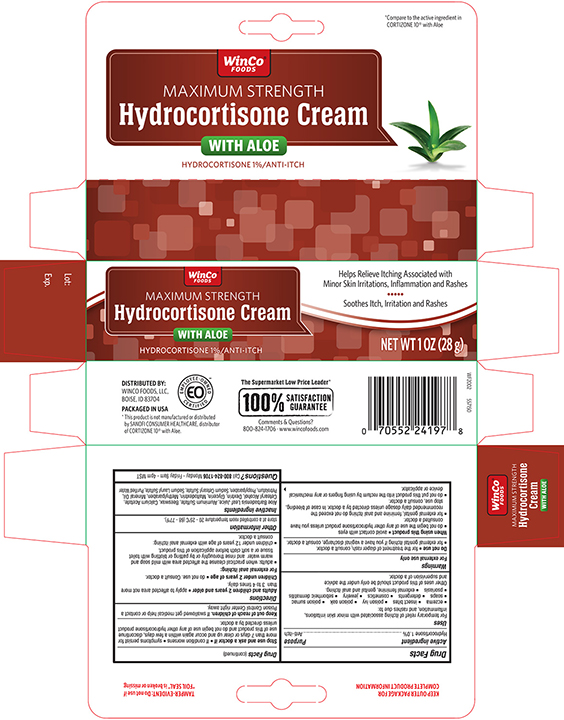 DRUG LABEL: WINCO Hydrocortisone
NDC: 67091-055 | Form: CREAM
Manufacturer: WinCo Foods LLC
Category: otc | Type: HUMAN OTC DRUG LABEL
Date: 20241121

ACTIVE INGREDIENTS: HYDROCORTISONE 10 mg/1 g
INACTIVE INGREDIENTS: ALOE VERA LEAF; ALUMINUM SULFATE; YELLOW WAX; CALCIUM ACETATE; CETOSTEARYL ALCOHOL; MALTODEXTRIN; GLYCERIN; METHYLPARABEN; MINERAL OIL; PETROLATUM; PROPYLPARABEN; SODIUM CETOSTEARYL SULFATE; SODIUM LAURETH SULFATE; WATER

Active Ingredient

Hydrocortisone 1.0%

Purpose

Anti-Itch

Uses

For temporary relief of itching associated with minor skin irritations, inflammation, and rashes due to:

- eczema
- insect bites
- poison ivy
- poison oak
- poison sumac
- soaps
- detergents
- cosmetics
- jewelry
- seborrheic dermatitis
- psoriasis
- external feminine, genital and anal itching.

Other uses of this product should be only under the advice and supervision of a doctor.

Warnings

For external use only

Do not use

- for the treatment of diaper rash, consult a doctor.
- for external genital itching if you have a vaginal discharge, consult a doctor.

When using this product

- avoid contact with eyes
- do not begin the use of any other hydrocortisone product unless you have consulted a doctor.
- for external genital, feminine and anal itching do not exceed the recommended daily dosage unless directed by a doctor. In case of bleeding, stop use, consult a doctor.
- do not put this product into the rectum by using fingers or any mechanical device or applicator.

Directions

- Adults and children 2 years and older
- apply to affected area not more than 3 to 4 times daily.

Stop use and ask a doctor if

- If condition worsens
- symptoms persist for more than 7 days or clear up and occur again within a few days, discontinue use of this product and do not begin use of any other hydrocortisone product unless directed by a doctor.

KEEP OUT OF REACH OF CHILDREN

Keep this and all drugs out of reach of children. If swallowed get medical help or contact a Poison Control Center right away.

INACTIVE INGREDIENT

Aloe Barbadensis Leaf Juice, Aluminum Sulfate, Beeswax, Calcium Acetate, Cetearyl Alcohol, Dextrin, Glycerin, Maltodextrin, Methylparaben, Mineral Oil, Petrolatum, Propylparaben, Sodium Cetearyl Sulfate, Sodium Lauryl Sulfate, Purified Water

Principal Display panel-Tube

WINCO NDC 67091-055-28

MAXIMUM STRENGTH

HYDROCORTISONE CREAM with aloe

Hydrocortisone 1%

NET WT. 1 OZ (28G)

Principal Display Panel - Carton

WINCO NDC 67091-055-28

MAXIMUM STRENGTH

HYDROCORTISONE CREAM with aloe

Hydrocortisone 1%

NET WT. 1 OZ (28G)